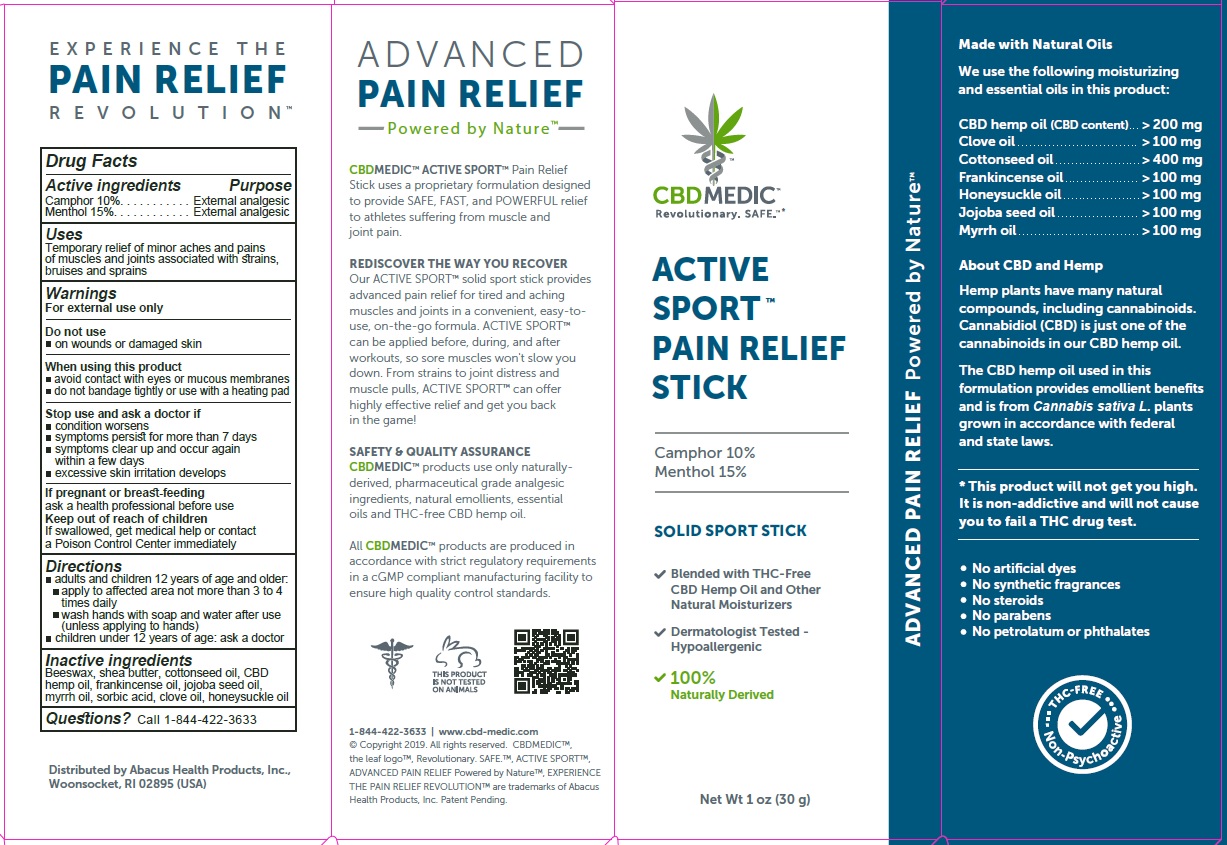 DRUG LABEL: CBDMEDIC Active Sport Pain Relief
NDC: 73096-741 | Form: STICK
Manufacturer: ABACUS HEALTH PRODUCTS, INC.
Category: otc | Type: HUMAN OTC DRUG LABEL
Date: 20250407

ACTIVE INGREDIENTS: CAMPHOR (NATURAL) 100 mg/1 g; MENTHOL 150 mg/1 g
INACTIVE INGREDIENTS: WHITE WAX; CLOVE OIL; COTTONSEED OIL; FRANKINCENSE OIL; HEMP; LONICERA CONFUSA WHOLE; JOJOBA OIL; MYRRH OIL; SHEA BUTTER; SORBIC ACID

CBDMEDIC Active Sport Pain Relief

Active Ingredients and Purpose

Camphor 10%, Menthol 15% (External Analgesics)

Uses

Temporary relief of minor aches and pains of muscles and joints associated with simple backache, arthritis, strains, bruises and sprains

Warnings

For external use only
Do not use on
• wounds or damaged skin
When using this product
• avoid contact with eyes or mucous membranes
• do not bandage tightly or use with a heating pad
Stop use and ask a doctor if
• condition worsens
• symptoms persist for more than 7 days
• symptoms clear up and occur again within a few days
• excessive skin irritation develops
If pregnant or breast-feeding
ask a health professional before use
Keep out of reach of children
If swallowed, get medical help or contact a Poison Control Center immediately

KEEP OUT OF REACH OF CHILDREN

If pregnant or breast-feeding

ask a health professional before use

Keep out of reach of children

If swallowed, get medical help or contact a Poison Control Center immediately

Directions

Adults and children 12 years of age and older:

• apply to affected area not more than 3 to 4 times daily

• Wash hands with soap and water after use (unless applying to hands)

Children under 12 years of age: ask a doctor

Inactive ingredients

Beeswax, shea butter, cottonseed oil, CBD hemp oil, frankincense oil, jojoba seed oil, myrrh oil, sorbic acid, clove oil, honeysuckle oil

Questions?

Call 1-844-422-3633